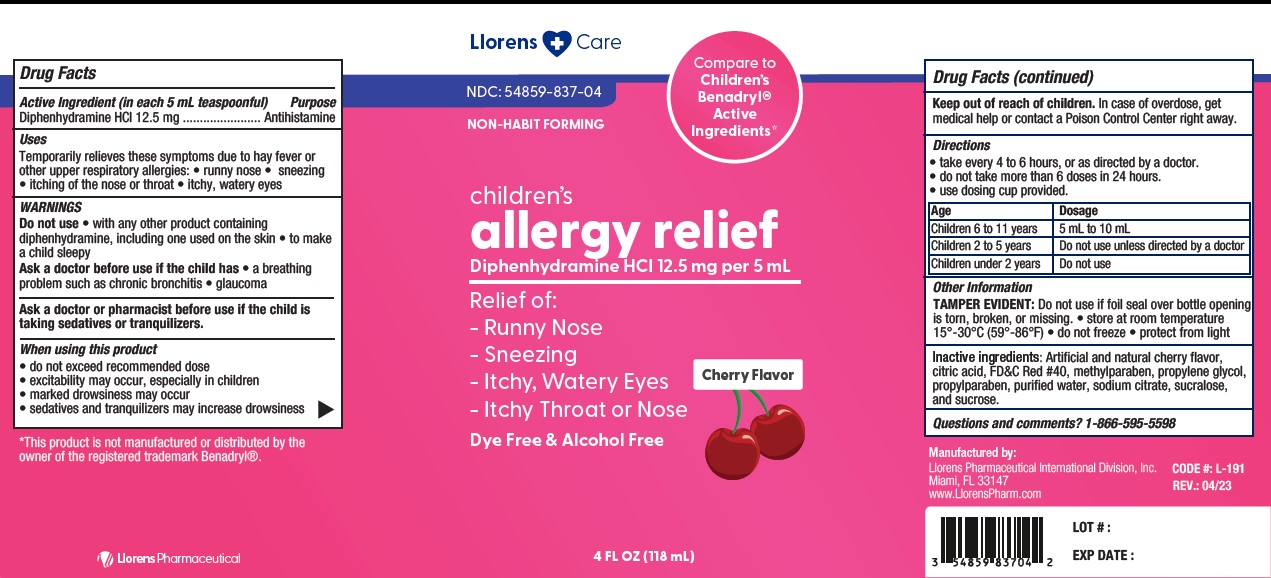 DRUG LABEL: Allergy Relief
NDC: 54859-837 | Form: LIQUID
Manufacturer: LLORENS PHARMACEUTICALS INTERNATIONAL DIVISION
Category: otc | Type: HUMAN OTC DRUG LABEL
Date: 20251231

ACTIVE INGREDIENTS: DIPHENHYDRAMINE HYDROCHLORIDE 12.5 mg/5 mL
INACTIVE INGREDIENTS: METHYLPARABEN; PROPYLENE GLYCOL; PROPYLPARABEN; WATER; SODIUM CITRATE; SUCRALOSE; SUCROSE; FD&C RED NO. 40; ANHYDROUS CITRIC ACID

Llorens-AllergyChild 837

Active ingredient (in each 5 mL teaspoonful)

Diphenhydramine HCl 12.5 mg

Purpose

Antihistamine

Uses

- Temporarily relieves these symptoms of hay fever or other upper respiratory allergies:
- runny nose
- sneezing
- itching of the nose or throat
- itchy, watery eyes

Warnings

Do not use

- with any other product conatining diphenhydramine, including one used on the skin
- to make a child sleepy

Ask a doctor before use if you have

- a breathing problem such as chronic bronchitis
- glaucoma

Ask a doctor or pharmacist before use if the child is

taking sedatives or tranquilizers.

When using this product

- do not exceed recommended dose
- excitability may occur, especially in children
- marked drowsiness may occur
- sedatives, and tranquilizers may increase drowsiness

PREGNANCY OR BREAST FEEDING

If pregnant or breast-feeding, ask a health professional before use.

Keep out of reach of children. In case of overdose, get medical help or contact a Poison Control Center right away.

Directions

- take every 4 to 6 hours as needed, or as directed by a doctor
- do not take more than 6 doses in 24 hours
- use dosing cup provided.

Age | Dosage
Children 6 to 11 years | 5 mL to 10 mL
Children2 to 5 years | Do not use unless directed by a doctor
Children under 2 years | Do not use

INACTIVE INGREDIENT

Inactive ingredients: Artificial and natural cherry flavor, citric acid, FD&C #40, methylparaben, propylene glycol, propylparaben, purified water, sodium citrate, sucralose and sucrose.

Questions or comments? 1-866-595-5598